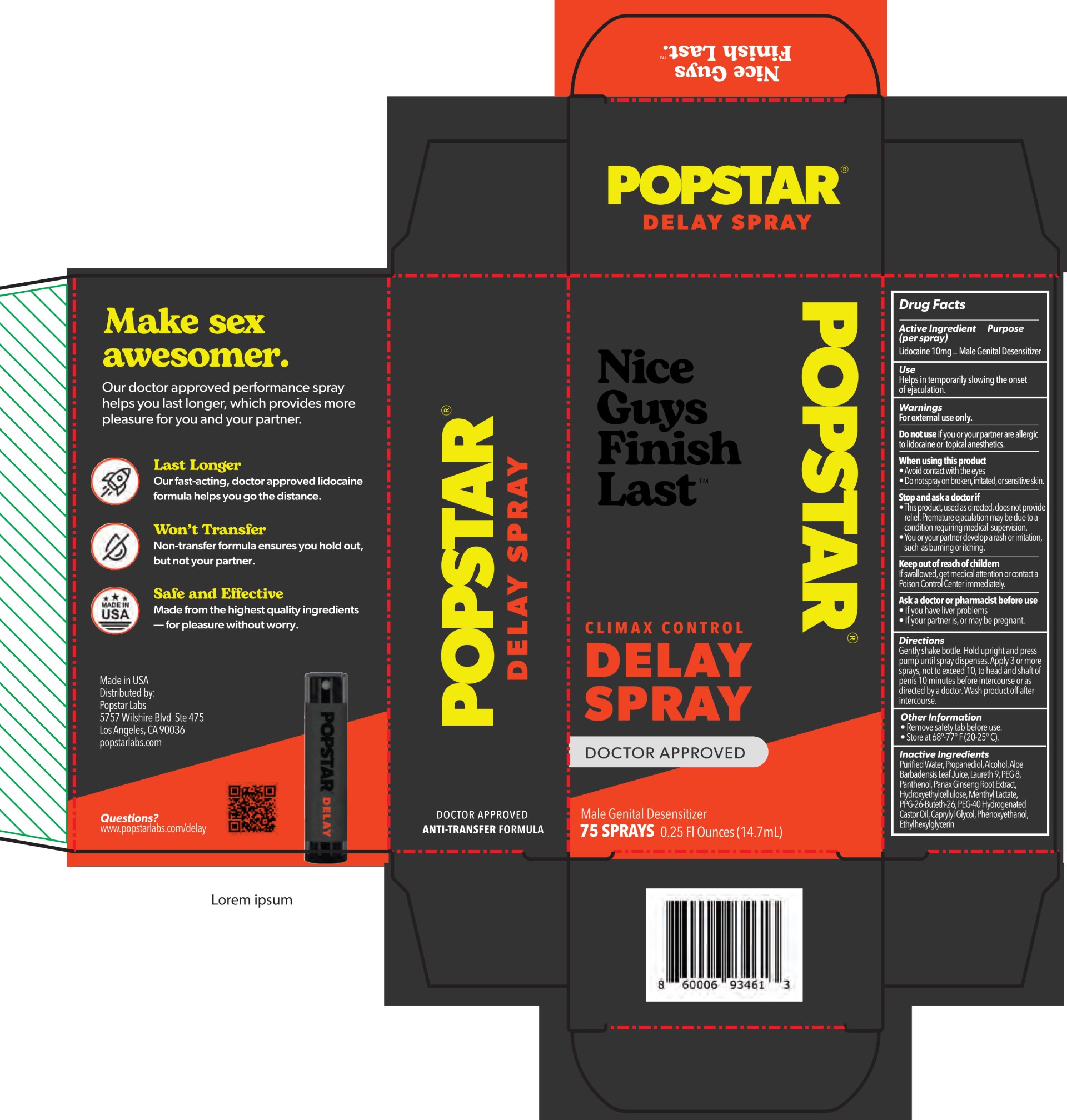 DRUG LABEL: Popstar
NDC: 85035-111 | Form: SPRAY
Manufacturer: Pineapple Brands LLC
Category: otc | Type: HUMAN OTC DRUG LABEL
Date: 20251212

ACTIVE INGREDIENTS: LIDOCAINE HYDROCHLORIDE 10 mg/100 mL
INACTIVE INGREDIENTS: HYDROXYETHYLCELLULOSE; PROPYLENE GLYCOL; MENTHYL LACTATE; ETHYLHEXYLGLYCERIN; PHENOXYETHANOL; WATER; LAURETH-9; ALCOHOL; ALOE VERA LEAF; PANAX GINSENG ROOT; PEG-40 HYDROGENATED CASTOR OIL; CAPRYLYL GLYCOL; PEG-8; PANTHENOL; PPG-26-BUTETH-26

Popstar Delay Spray 14.7 mL

Active Ingredient(s)

Lidocaine 10mg .. Male Genital Desensitizer

Purpose

Male Genital Desensitizer

Use

Helps in temporarily slowing the onset of ejaculation.

Warnings

For external use only.

Do not use if you or your partner are allergic to lidocaine or topical anesthetics.

When using this product

Avoid contact with the eyes
Do not spray on broken, irritated, or sensitive skin.

Stop and ask a doctor if

This product, used as directed, does not provide relief. Premature ejaculation may be due to a condition requiring medical supervision.
You or your partner develop a rash or irritation, such as burning or itching.

Ask a doctor or pharmacist before use

If you have liver problems
If your partner is, or may be pregnant.

Keep out of reach of childern

If swallowed, get medical attention or contact a Poison Control Center immediately.

Directions

Gently shake bottle. Hold upright and press the pump until the spray dispenses. Apply 3 or more sprays, not to exceed 10, to head and shaft of penis 10 minutes betore intercourse or as directed by a doctor. Wash the product off after intercourse.

Other information

Remove safety tab before use.
Store at 68°-77° F (20-25° C).

Inactive ingredients

Purified Water, Propanediol, Alcohol, Aloe Barbadensis Leaf Juice, Laureth 9, PEG 8, Panthenol, Panax Ginseng Root Extract, Hydroxyethylcellulose, Menthyl Lactate, PPG-26-Buteth-26, PEG-40 Hydrogenated Castor Oil, Caprylyl Glycol, Phenoxyethanol,

Ethylhexylglycerin